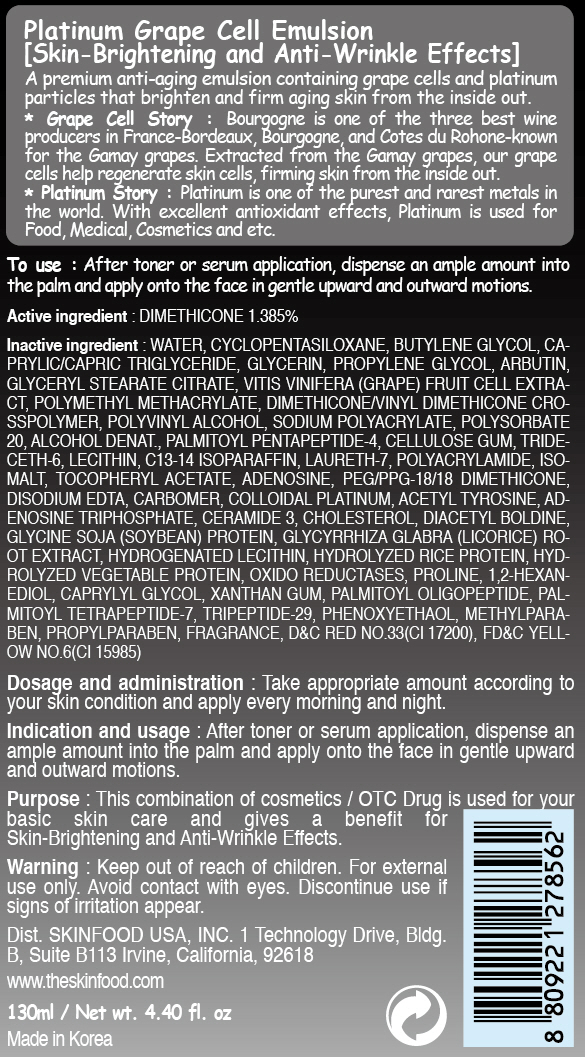 DRUG LABEL: PLATINUM GRAPE CELL EMULSION
NDC: 76214-008 | Form: CREAM
Manufacturer: SKINFOOD CO., LTD.
Category: otc | Type: HUMAN OTC DRUG LABEL
Date: 20110727

ACTIVE INGREDIENTS: DIMETHICONE 1.8 mL/130 mL
INACTIVE INGREDIENTS: WATER; CYCLOMETHICONE 5; BUTYLENE GLYCOL; GLYCERIN; PROPYLENE GLYCOL; ARBUTIN; GLYCERYL STEARATE CITRATE; WINE GRAPE; POLYVINYL ALCOHOL; SODIUM POLYACRYLATE (2500000 MW); PHENOXYETHANOL; POLYSORBATE 20; METHYLPARABEN; PALMITOYL PENTAPEPTIDE-4; CARBOXYMETHYLCELLULOSE SODIUM; PROPYLPARABEN; TRIDECETH-6; LECITHIN, SOYBEAN; C13-14 ISOPARAFFIN; LAURETH-7; ISOMALT; ADENOSINE; EDETATE DISODIUM; ADENOSINE TRIPHOSPHATE; CERAMIDE 3; CHOLESTEROL; GLYCYRRHIZA GLABRA; HYDROGENATED SOYBEAN LECITHIN; PROLINE; 1,2-HEXANEDIOL; CAPRYLYL GLYCOL; XANTHAN GUM; PALMITOYL OLIGOPEPTIDE; PALMITOYL TETRAPEPTIDE-7

Drug Facts

Active ingredient: DIMETHICONE 1.385%

Inactive ingredients:

WATER, CYCLOPENTASILOXANE, BUTYLENE GLYCOL, CAPRYLIC/CAPRIC TRIGLYCERIDE, GLYCERIN, PROPYLENE GLYCOL, ARBUTIN, GLYCERYL STEARATE CITRATE,
VITIS VINIFERA (GRAPE) FRUIT CELL EXTRACT, POLYMETHYL METHACRYLATE, DIMETHICONE/VINYL DIMETHICONE CROSSPOLYMER, POLYVINYL ALCOHOL, SODIUM POLYACRYLATE, POLYSORBATE 20, ALCOHOL DENAT., PALMITOYL PENTAPEPTIDE-4, CELLULOSE GUM, TRIDECETH-6, LECITHIN, C13-14 ISOPARAFFIN, LAURETH-7, POLYACRYLAMIDE, ISOMALT, TOCOPHERYL ACETATE, ADENOSINE, PEG/PPG-18/18 DIMETHICONE, DISODIUM EDTA, CARBOMER, COLLOIDAL PLATINUM, ACETYL TYROSINE, ADENOSINE TRIPHOSPHATE, CERAMIDE 3, CHOLESTEROL, DIACETYL BOLDINE, GLYCINE SOJA (SOYBEAN) PROTEIN, GLYCYRRHIZA GLABRA (LICORICE) ROOT EXTRACT, HYDROGENATED LECITHIN, HYDROLYZED RICE PROTEIN, HYDROLYZED VEGETABLE PROTEIN, OXIDO REDUCTASES, PROLINE, 1,2-HEXANEDIOL, CAPRYLYL GLYCOL, XANTHAN GUM, PALMITOYL OLIGOPEPTIDE, PALMITOYL TETRAPEPTIDE-7, TRIPEPTIDE-29, PHENOXYETHANOL, METHYLPARABEN, PROPYLPARABEN, FRAGRANCE

Purpose:

This combination of cosmetics is used for your basic skin care and gives a benefit for Skin-Brightening and Anti-Wrinkle Effects.

Warnings:

For external use only. Avoid contact with eyes. Discontinue use if signs of irritation appear.

Keep out of reach of children:

Keep out of reach of children.

Indication and usage:

After toner or serum application, dispense an ample amount into the palm and apply onto the face in gentle upward and outward motions.

Dosage and administration:

Take appropriate amount according to your skin condition and apply every morning and night.